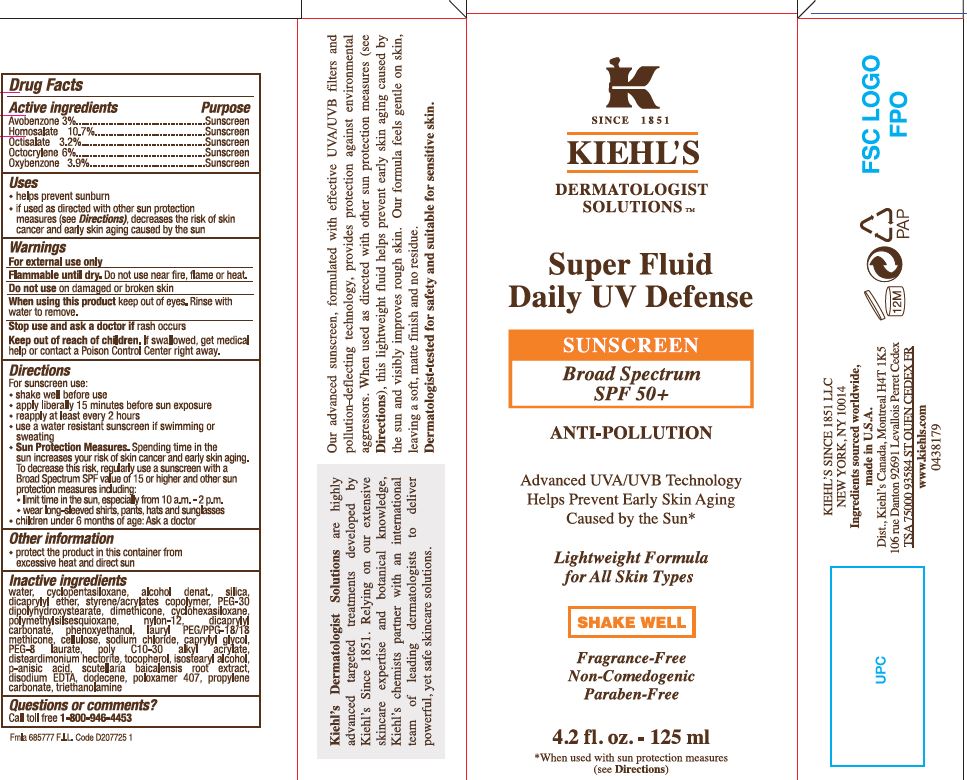 DRUG LABEL: Kiehls Super Fluid Daily UV Defense SPF 50 plus Anti-Pollution Lightweight Formula for All Skin Types
NDC: 49967-181 | Form: CREAM
Manufacturer: L'Oreal USA Products Inc
Category: otc | Type: HUMAN OTC DRUG LABEL
Date: 20240101

ACTIVE INGREDIENTS: AVOBENZONE 30 mg/1 mL; HOMOSALATE 107 mg/1 mL; OCTISALATE 32 mg/1 mL; OCTOCRYLENE 60 mg/1 mL; OXYBENZONE 39 mg/1 mL
INACTIVE INGREDIENTS: WATER; CYCLOMETHICONE 5; ALCOHOL; SILICON DIOXIDE; DICAPRYLYL ETHER; STYRENE/ACRYLAMIDE COPOLYMER (500000 MW); PEG-30 DIPOLYHYDROXYSTEARATE; DIMETHICONE; CYCLOMETHICONE 6; POLYMETHYLSILSESQUIOXANE (11 MICRONS); NYLON-12; DICAPRYLYL CARBONATE; PHENOXYETHANOL; LAURYL PEG/PPG-18/18 METHICONE; POWDERED CELLULOSE; SODIUM CHLORIDE; CAPRYLYL GLYCOL; PEG-8 LAURATE; DISTEARDIMONIUM HECTORITE; TOCOPHEROL; ISOSTEARYL ALCOHOL; P-ANISIC ACID; SCUTELLARIA BAICALENSIS ROOT; EDETATE DISODIUM; dodecene; POLOXAMER 407; PROPYLENE CARBONATE; TROLAMINE

Drug Facts

Active ingredients

Avobenzone 3%

Homosalate 10.7%

Octisalate 3.2%

Octocrylene 6%

Oxybenzone 3.9%

Purpose

Sunscreen

Uses

- helps prevent sunburn
- if used as directed with other sun protection measures (see Directions), decreases the risk of skin cancer and early skin aging caused by the sun

Warnings

For external use only

Flammble until dry. Do not use near fire, flame or heat.

Do not use

on damaged or broken skin

When using this product

keep out of eyes. Rinse with water to remove.

Stop use and ask a doctor if

rash occurs

Keep out of reach of children.

If swallowed, get medical help or contact a Poison Control Center right away.

Directions

- shake well before use
- apply liberally 15 minutes before sun exposure
- reapply at least every 2 hours
- use a water resistant sunscreen if swimming or sweating
- Sun Protection Measures. Spending time in the sun increases your risk of skin cancer and early skin aging. To decrease this risk, regularly use a sunscreen with a Broad Spectrum SPF value of 15 or higher and other sun protection measures including:
- limit time in the sun, especially from 10 a.m. - 2p.m.
- wear long-sleeved shirts, pants, hats and sunglasses
- children under 6 months of age: Ask a doctor

Other information

- protect the product in this container from excessive heat and direct sun

Inactive ingredients

water, cyclopentasiloxane, alcohol denat., silica, dicaprylyl ether, styrene/acrylates copolymer, PEG-30 dipolyhydroxystearate, dimethicone, cyclohexasiloxane, polymethylsilsequioxane, nylon-12, dicaprylyl carbonate, phenoxyethanol, lauryl PEG/PPG- 18/18 methicone, cellulose, sodium chloride, caprylyl glycol, PEG-8 laurate, poly C10-30 alkyl acrylate, disteardimonium hectorite, tocopherol, isostearyl alcohol, p-anisic acid, scutellaria baicalensis root extract, disodium EDTA, dodecene, poloxamer 407, propylene carbonate, triethanolamine